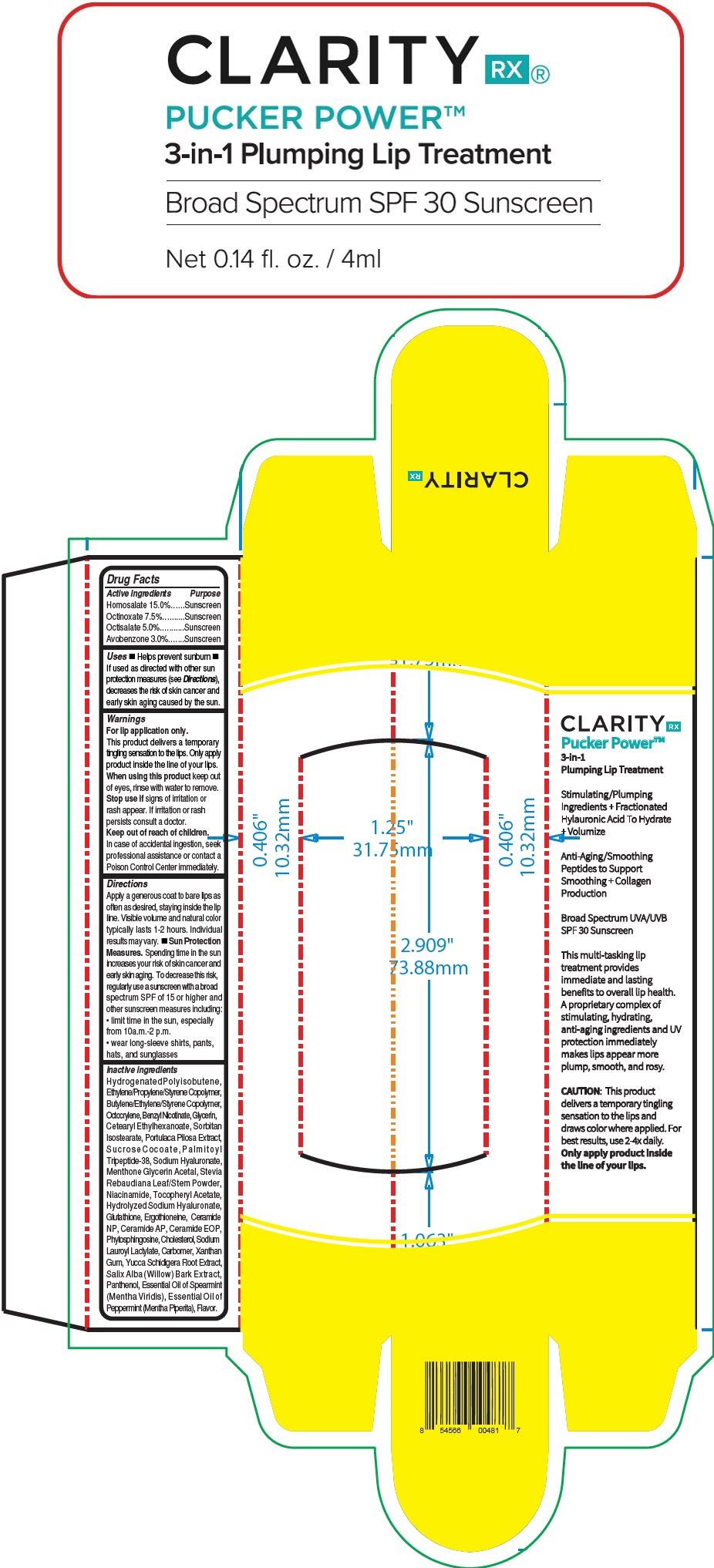 DRUG LABEL: Clarity Rx Pucker Power lip plumper
NDC: 51326-001 | Form: LIPSTICK
Manufacturer: Topiderm, Inc.
Category: otc | Type: HUMAN OTC DRUG LABEL
Date: 20240731

ACTIVE INGREDIENTS: HOMOSALATE 150 mg/1 g; OCTINOXATE 75 mg/1 g; OCTISALATE 50 mg/1 g; AVOBENZONE 30 mg/1 g
INACTIVE INGREDIENTS: HYDROGENATED POLYISOBUTENE (1300 MW); OCTOCRYLENE; BENZYL NICOTINATE; GLYCERIN; .ALPHA.-TOCOPHEROL ACETATE; GLUTATHIONE; ERGOTHIONEINE; YUCCA GLAUCA ROOT; SALIX ALBA BARK; CERAMIDE NP; CERAMIDE AP; CERAMIDE 1; HYALURONATE SODIUM; NIACINAMIDE; PHYTOSPHINGOSINE; SPEARMINT OIL; MENTHA ARVENSIS LEAF OIL; PEPPERMINT OIL; PALMITOYL TRIPEPTIDE-38; CHOLESTEROL; STEVIA REBAUDIUNA LEAF; SUCROSE COCOATE; PANTHENOL; SODIUM LAUROYL LACTYLATE; MENTHONE 1,2-GLYCEROL KETAL, (+/-)-; CARBOMER HOMOPOLYMER, UNSPECIFIED TYPE; XANTHAN GUM; CETEARYL ETHYLHEXANOATE; SORBITAN ISOSTEARATE; PHENOXYETHANOL; ETHYLHEXYLGLYCERIN; WATER; STYRENE/ISOPRENE COPOLYMER (28:72; 210000 MW)

Clarity Rx® Pucker Power™ lip plumper
SPF 30

Drug Facts

ACTIVE INGREDIENT

Active ingredients | Purpose
Homosalate 15.0% | Sunscreen
Octinoxate 7.5% | Sunscreen
Octisalate 5.0% | Sunscreen
Avobenzone 3.0% | Sunscreen

Uses

- Helps prevent sunburn
- If used as directed with other sun protection measures (see Directions), decreases the risk of skin cancer and early skin aging caused by the sun.

Warnings

For lip application only.

This product delivers a temporary tingling sensation to the lips. Only apply product inside the line of your lips.

When using this product keep out of eyes, rinse with water to remove.

Stop use if signs of irritation or rash appear. If irritation or rash persists consult a doctor.

Keep out of reach of children.

In case of accidental ingestion, seek professional assistance or contact a Poison Control Center immediately.

Directions

Apply a generous coat to bare lips as often as desired, staying inside the lip line. Visible volume and natural color typically lasts 1-2 hours. Individual results may vary.

- Sun Protection Measures. Spending time in the sun increases your risk of skin cancer and early skin aging. To decrease this risk, regularly use a sunscreen with a broad spectrum SPF of 15 or higher and other sunscreen measures including:
  - limit time in the sun, especially from 10a.m.-2 p.m.
  - wear long-sleeve shirts, pants, hats, and sunglasses

Inactive ingredients

Hydrogenated Polyisobutene, Ethylene/Propylene/Styrene Copolymer, Butylene/Ethylene/Styrene Copolymer, Octocrylene, Benzyl Nicotinate, Glycerin, Cetearyl Ethylhexanoate, Sorbitan Isostearate, Portulaca Pilosa Extract, Sucrose Cocoate, Palmitoyl Tripeptide-38, Sodium Hyaluronate, Menthone Glycerin Acetal, Stevia Rebaudiana Leaf/Stem Powder, Niacinamide, Tocopheryl Acetate, Hydrolyzed Sodium Hyaluronate, Glutathione, Ergothioneine, Ceramide NP, Ceramide AP, Ceramide EOP, Phytosphingosine, Cholesterol, Sodium Lauroyl Lactylate, Carbomer, Xanthan Gum, Yucca Schidigera Root Extract, Salix Alba (Willow) Bark Extract, Panthenol, Essential Oil of Spearmint (Mentha Viridis), Essential Oil of Peppermint (Mentha Piperita), Flavor.

PRINCIPAL DISPLAY PANEL - 4 ml Tube Box

CLARITY RX®

PUCKER POWER™

3-in-1 Plumping Lip Treatment

Broad Spectrum SPF 30 Sunscreen

Net 0.14 fl. oz. / 4ml